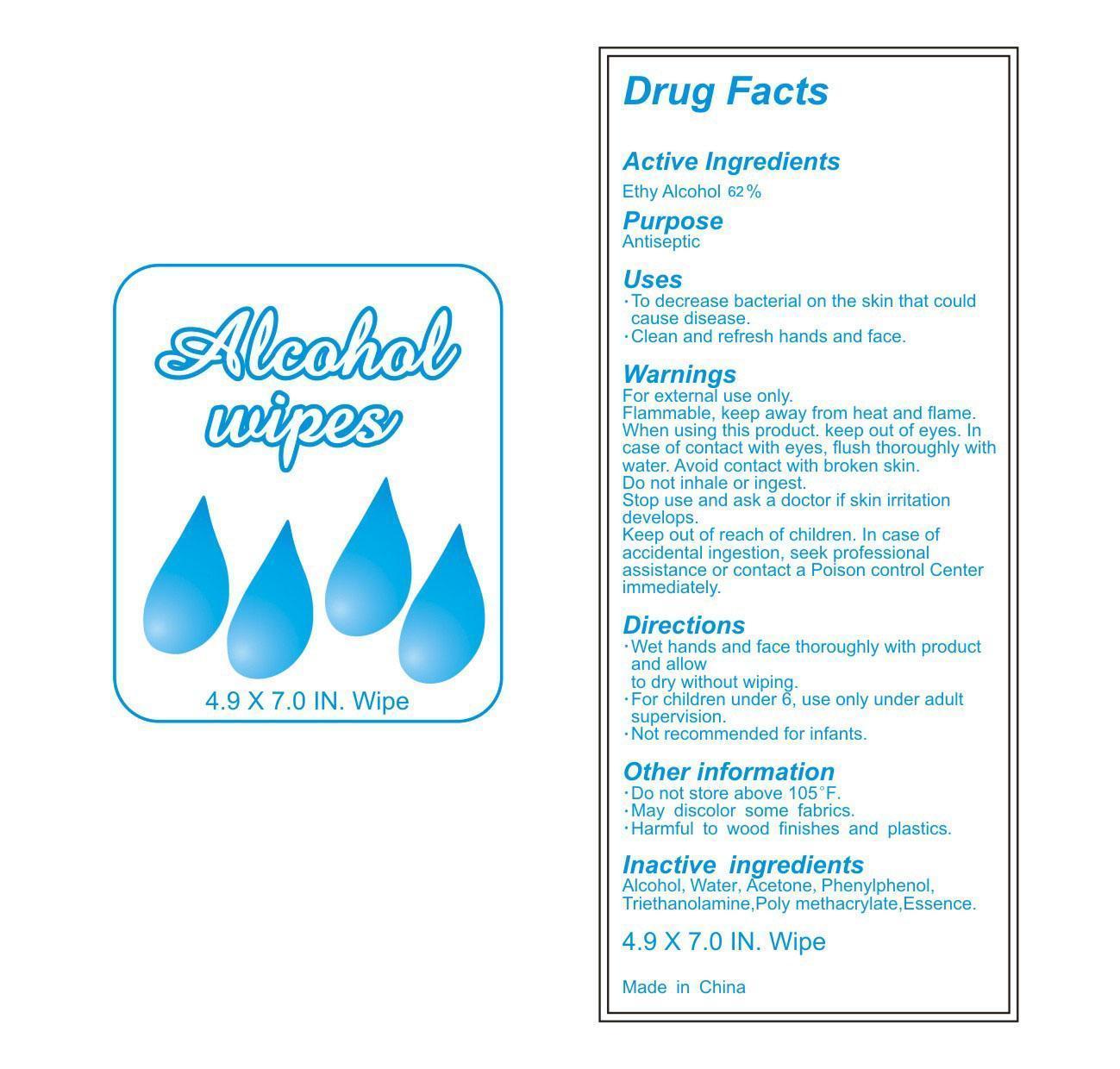 DRUG LABEL: Alcohol Wipes
NDC: 42869-803 | Form: CLOTH
Manufacturer: Jiangmen Nowadays Daily Goods Co., Ltd.
Category: otc | Type: HUMAN OTC DRUG LABEL
Date: 20150831

ACTIVE INGREDIENTS: Alcohol .62 mL/1 mL
INACTIVE INGREDIENTS: Aloe Vera Leaf; Propylene Glycol; Water

DRUG FACTS

Active Ingredient

Ethyl Alcohol 31% (v/v)

Purpose

Antiseptic

Uses:

- To decrease bacterial on the skin that could cause disease.
- Clean and refresh hands and face.

WARNINGS

For external use only.

DO NOT USE

- Flammable, keep away from heat and flame.
- When using this product, keep out of eyes. In case of eye contact, flush thoroughly with water.
- Avoid contact with broken skin.
- Do not inhale or ingest.
- Stop use and ask a doctor if skin irritation develops.

Keep out of reach of children.

In case of accidental ingestion, seekprofessional assistance or contact a Poison Control Center immediately.

Directions:

- Wet hands and face thoroughly with product and allow to dry without wiping
- For children under 6, use only under adult supervision.
- Not recommended for infants.

Inactive Ingredients:

water, acetone, phenylphenol, triethanolamine, poly methacrylate, essence